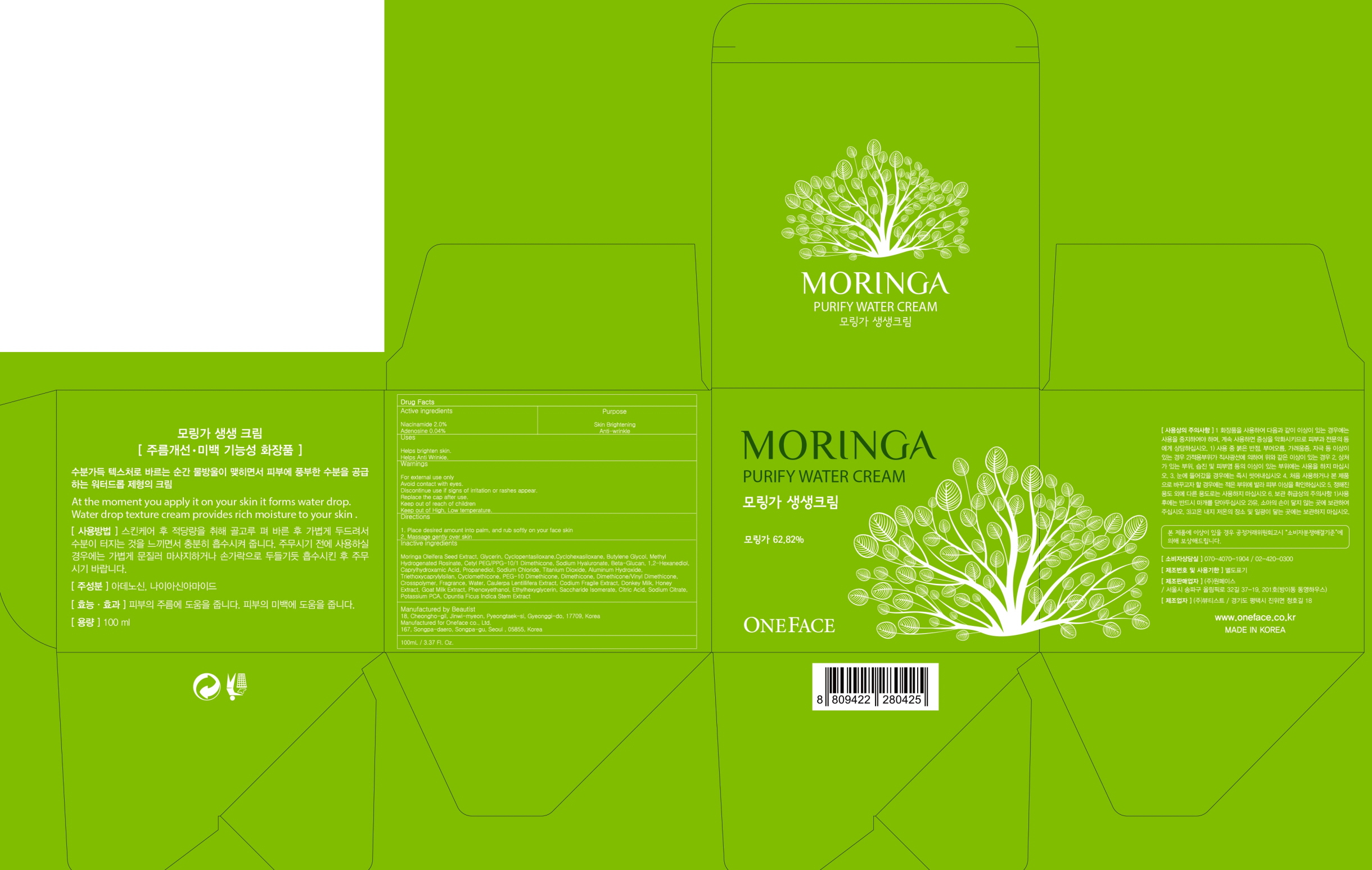 DRUG LABEL: MORINGA PURIFY WATER
NDC: 72255-010 | Form: CREAM
Manufacturer: Oneface co., Ltd.
Category: otc | Type: HUMAN OTC DRUG LABEL
Date: 20180510

ACTIVE INGREDIENTS: Niacinamide 2.0 g/100 mL; Adenosine 0.04 g/100 mL
INACTIVE INGREDIENTS: Glycerin; Butylene Glycol

ACTIVE INGREDIENT

Active ingredients: Niacinamide 2.0%, Adenosine 0.04%

INACTIVE INGREDIENT

Inactive ingredients:

Moringa Oleifera Seed Extract, Glycerin, Cyclopentasiloxane, Cyclohexasiloxane, Butylene Glycol, Methyl Hydrogenated Rosinate, Cetyl PEG/PPG-10/1 Dimethicone, Sodium Hyaluronate, Beta-Glucan, 1,2-Hexanediol, Caprylhydroxamic Acid, Propanediol, Sodium Chloride, Titanium Dioxide, Aluminum Hydroxide, Triethoxycaprylylsilan, Cyclomethicone, PEG-10 Dimethicone, Dimethicone, Dimethicone/Vinyl Dimethicone, Crosspolymer, Fragrance, Water, Caulerpa Lentillifera Extract, Codium Fragile Extract, Donkey Milk, Honey Extract, Goat Milk Extract, Phenoxyethanol, Ethylhexyglycerin, Saccharide Isomerate, Citric Acid, Sodium Citrate, Potassium PCA, Opuntia Ficus Indica Stem Extract

PURPOSE

Purpose: Skin Brightening, Anti-wrinkle

WARNINGS

For external use only

Avoid contact with eyes.

Discontinue use if signs of irritation or rashes appear.

Replace the cap after use.

Keep out of reach of children

Keep out of High, Low temperature.

KEEP OUT OF REACH OF CHILDREN

Uses

Helps brighten skin. Helps anti wrinkle.

Directions

1. Place desired amount into palm, and rub softly on your face skin

2. Massage gently over skin